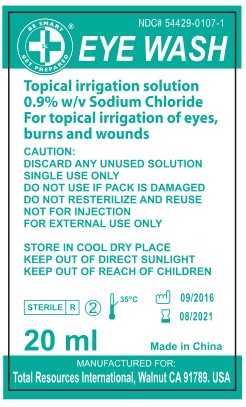 DRUG LABEL: EYE WASH
NDC: 54429-0107 | Form: LIQUID
Manufacturer: Foshan Flying Medical Products Co., Ltd.
Category: otc | Type: HUMAN OTC DRUG LABEL
Date: 20160914

ACTIVE INGREDIENTS: WATER 99.1 mL/100 mL
INACTIVE INGREDIENTS: SODIUM CHLORITE

EYE WASH

Active ingredient Purpose

Purified water (99.1%)..................................... Eyewash

PURPOSE

Eye wash

INSTRUCTIONS FOR USE

- To pour - hold bottle securely, twist off top to remove
- Control rate of flow by pressure on the bottle
- Flush the affected eye(s) as needed
- Do not touch bottle tip to eye
- If necessary, continue flushing with emergency eyewash or shower.

Do not use if pack is damaged

Do not use resterilize and reuse

DOSAGE AND ADMINISTRATION

Topical irrigation solution

0.9% w/v Sodium Chloride

INDICATIONS AND USAGE

For topical irrigation of eyes, burns and wounds

INACTIVE INGREDIENT

0.9% w/v Sodium Chloride

OTHER SAFETY INFORMATION

Caution:

Discard any unused solution

Single use only

STORAGE AND HANDLING

Store in cool dry place

Keep out of direct sunlight

Keep out of reach of children

Keep out of reach of children

PACKAGE LABEL

NDC# 54429-0107-1

EYE WASH

Topical irrigation solution 0.9% w/v Sodium Chloride

For topical irrigation of eyes, burns and wounds

CAUTION:

DISCARD ANY UNUSED SOLUTION

SINGLE USE ONLY

DO NOT USE IF PACK IS DAMAGED

DO NOT RESTERILIZE AND REUSE

NOT FOR INJECTION

FOR EXTERNAL USE ONLY

STORE IN COOL DRY PLACE

KEEP OUT OF DIRECT SUNLIGHT

KEEP OUT OF REACH OF CHILDREN

20 ml

Made in China

MANUFACTURED FOR:

Total Resources Intenational, Walnut CA 91789. USA